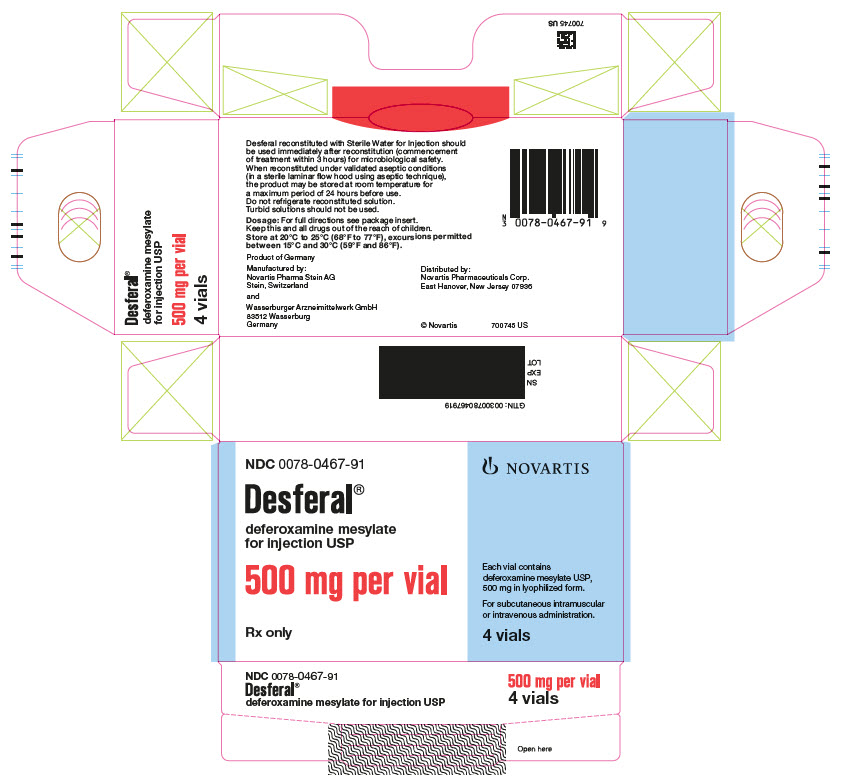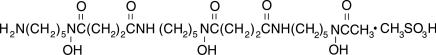 DRUG LABEL: Desferal
NDC: 0078-0467 | Form: INJECTION, POWDER, LYOPHILIZED, FOR SOLUTION
Manufacturer: Novartis Pharmaceuticals Corporation
Category: prescription | Type: HUMAN PRESCRIPTION DRUG LABEL
Date: 20250617

ACTIVE INGREDIENTS: DEFEROXAMINE MESYLATE 500 mg/1 1

HIGHLIGHTS OF PRESCRIBING INFORMATION

These highlights do not include all the information needed to use DESFERAL safely and effectively. See full prescribing information for DESFERAL.
DESFERAL® (deferoxamine mesylate) for injection, for intramuscular, intravenous, or subcutaneous use
Initial U.S. Approval: 1968

1 INDICATIONS AND USAGE

DESFERAL is an iron-chelating agent indicated:

- As an adjunct to standard measures for the treatment of acute iron intoxication. (1.1)
- For the treatment of transfusional iron overload in patients with chronic anemia. (1.2)

Limitations of Use (1.3)

Desferal is not indicated for the treatment of primary hemochromatosis (since phlebotomy is the method of choice for removing excess iron in this disorder).

2 DOSAGE AND ADMINISTRATION

Acute Iron Intoxication: (2.1)

- Intramuscular Administration: Use for patients not in shock. Initial dose is 1,000 mg. Depending upon the clinical response, subsequent doses of 500 mg may be administered every 4 hours to 12 hours. Maximum dose is 6,000 mg in 24 hours.
- Intravenous Administration: Only for patients in a state of cardiovascular collapse. Initial dose is 1,000 mg at a rate not to exceed 15 mg/kg/hr. Depending upon the clinical response, subsequent doses of 500 mg may be administered every 4 hours to 12 hours at a rate of up to 125 mg/hr. Maximum dose is 6,000 mg in 24 hours.

Chronic Iron Overload: (2.2)

- Subcutaneous Infusion: Average daily dose is between 20 and 60 mg/kg. In patients with serum ferritin level below 2,000 ng/mL require about 25 mg/kg/day. Patients with serum ferritin level between 2,000 and 3,000 ng/mL require about 35 mg/kg/day. Patients with higher serum ferritin may require up to 55 mg/kg/day.
- Intravenous Administration: 20 mg/kg/day to 40 mg/kg/day for pediatric patients and 40 mg/kg/day to 50 mg/kg/day over 8 hours to 12 hours in adults for 5 days to 7 days per week. In pediatric patients and adults, maximum dose should not exceed 40 mg/kg/day and 60 mg/kg/day, respectively.
- Intramuscular Administration: 500 mg to maximum daily dose of 1,000 mg.

See Full Prescribing Information for instructions on preparation of Desferal for administration. (2.3)

Vitamin C (up to 200 mg) increases availability of iron for chelation and may be given as an adjuvant to iron chelation therapy. (2.4)

3 DOSAGE FORMS AND STRENGTHS

For injection: 500 mg of deferoxamine mesylate as a lyophilized powder in single-dose vial for reconstitution. (3)

4 CONTRAINDICATIONS

- Known hypersensitivity to the active substance. (4)
- Patients with severe renal disease or anuria. (4)

5 WARNINGS AND PRECAUTIONS

- Hypersensitivity Reactions: More common with rapid intravenous infusion. Administer intramuscularly or by slow subcutaneous or intravenous infusion. (5.1)
- Auditory and Ocular Toxicity: Have been reported when administered over prolonged periods of time, at high doses, or in patients with low ferritin levels. (5.2)
- Renal Toxicity: Cases of acute renal failure, renal tubular disorders and increase in serum creatinine have occurred. Monitor patients for changes in renal function. (5.3)
- Respiratory Toxicity: Acute respiratory distress syndrome has occurred. Risk increased with high intravenous doses. Recommended daily dose should not be exceeded. (5.4)
- Growth Suppression: Has occurred in pediatric patients treated with high doses and concomitant low ferritin levels. Dose reduction may partially resume growth velocity to pre-treatment rates. (5.5)
- Serious Infections: Cases of mucormycosis and Yersinia infections, some fatal, have occurred. Discontinue Desferal and initiate appropriate treatment immediately. (5.6)
- Cardiac Dysfunction with Concomitant Use of Vitamin C: Avoid coadministration in patients with cardiac failure. Delay Vitamin C for one month after start of Desferal. Avoid exceeding 200 mg daily in adults. Monitor cardiac function with combined treatment. (5.7)
- Risks of Desferal Treatment in Patients with Aluminum Overload: Risks include neurological dysfunction (including seizures), dialysis dementia, and aggravation of hyperparathyroidism. (5.8)
- Effects on Ability to Drive and Use Machines: May cause dizziness. (5.9)
- Embryo-Fetal Toxicity: Can cause fetal harm. Advise females of reproductive potential of the potential risk to a fetus and use effective contraception. (5.10, 8.1, 8.3)

6 ADVERSE REACTIONS

Most common adverse reactions are injection reactions (local and systemic), hypersensitivity reactions, infections with Yersinia and Mucormycosis, cardiovascular, gastrointestinal, hematologic, hepatic, musculoskeletal, urogenital, nervous, respiratory, ocular and hearing. (6)

To report SUSPECTED ADVERSE REACTIONS, contact Novartis Pharmaceuticals Corporation at 1-888-669-6682 or FDA at 1-800-FDA-1088 or www.fda.gov/medwatch.

7 DRUG INTERACTIONS

- Concurrent treatment with prochlorperazine may lead to temporary impairment of consciousness. (7.1)
- Imaging results may be distorted due to rapid urinary excretion of Desferal bound gallium-67. Discontinue Desferal 48 hours prior to scintigraphy. (7.2)

8 USE IN SPECIFIC POPULATIONS

- Lactation: Advise not to breastfeed (8.2)
- Geriatric Use: Increased risk of ocular disorders (8.5)

FULL PRESCRIBING INFORMATION

1 INDICATIONS AND USAGE

1.1 Acute Iron Intoxication

DESFERAL is indicated as an adjunct to standard measures for the treatment of acute iron intoxication.

1.2 Chronic Iron Overload

DESFERAL is indicated for the treatment of transfusional iron overload in patients with chronic anemia.

1.3 Limitations of Use

Desferal is not indicated for the treatment of primary hemochromatosis (since phlebotomy is the method of choice for removing excess iron in this disorder).

2 DOSAGE AND ADMINISTRATION

The dosage (based on body weight in mg/kg/day), rates of administration, and mode of administration for both adults and pediatric patients are individually determined and adapted during the course of therapy based on the severity of the patient's iron overload. The minimum daily dose of Desferal is 20 mg/kg/day for both adults and pediatric patients. The maximum daily dose is 40 mg/kg/day for pediatric patients and 60 mg/kg/day for adults.

2.1 Recommended Dosage for Treatment of Acute Iron Intoxication for Adults and Pediatric Patients

Intramuscular Administration

Use for all patients not in shock.

The initial recommended dose of Desferal is 1,000 mg intramuscularly once. If needed based on the clinical response, administer subsequent doses of 500 mg every 4 hours to 12 hours. The maximum recommended daily dose is 6,000 mg in 24 hours.

Intravenous Administration

Administer Desferal intravenously to patients in a state of cardiovascular collapse and then only by slow infusion. As soon as the clinical condition of the patient permits, intravenous administration should be discontinued, and the drug should be administered intramuscularly.

The initial recommended IV dose of Desferal is 1,000 mg administered at an infusion rate of up to 15 mg/kg/hr. If needed based on the clinical response administer additional doses of 500 mg over 4 hours to 12 hours at a slower infusion rate of up to 125 mg/hr. The maximum recommended daily dose is 6,000 mg in 24 hours.

2.2 Recommended Dosage for Treatment of Chronic Iron Overload for Adults and Pediatric Patients

Subcutaneous Infusion Administration

The average daily dose of Desferal is usually between 20 and 60 mg/kg. In general patients with serum ferritin level below 2,000 ng/mL require about 25 mg/kg/day. Patients with serum ferritin level between 2,000 and 3,000 ng/mL require about 35 mg/kg/day. Patients with higher serum ferritin may require up to 55 mg/kg/day. It is not advisable to regularly exceed an average daily dose of 50 mg/kg/day except when very intensive chelation is needed in patients who have completed growth. If ferritin levels fall below 1,000 ng/mL, the risk of Desferal toxicity increases; it is important to monitor these patients particularly carefully and perhaps to consider lowering the total weekly dose. The doses specified here are the average daily doses. Since most patients use Desferal less than 7 days a week, the actual dose per infusion usually differs from the average daily dose; e.g., if an average daily dose of 40 mg/kg/day is required and the patient wears the pump 5 nights a week, each infusion should contain 56 mg/kg.

Slow subcutaneous infusion using a portable, light-weight infusion pump over a period of 8 to 12 hours is regarded as effective and especially convenient for ambulatory patients but may also be given over a 24-hour period. Desferal should normally be used with the pump 5 to 7 times a week. Desferal is not formulated to support subcutaneous bolus injection.

Intravenous Administration

Desferal can be administered intravenously if needed in patients with intravenous access.

The recommended dose of Desferal in adults is 40 mg/kg/day to 50 mg/kg/day over 8 hours to 12 hours at a rate of up to 15 mg/kg/hour for 5 days to 7 days per week. Maximum dose is 60 mg/kg/day.

The recommended dose of Desferal in pediatric patients is 20 mg/kg/day to 40 mg/kg/day over 8 hours to 12 hours for 5 days to 7 days per week. The maximum recommended daily dose is 40 mg/kg/day until growth (body weight and linear growth) has ceased.

In case of missed doses, Desferal may be administered prior to or following same day blood transfusion (for example, 1 gram over 4 hours on the day of transfusion); however, the contribution of this mode of administration to iron balance is limited. Desferal should not be administered concurrently with the blood transfusion as this can lead to errors in interpreting side effects such as rash, anaphylaxis and hypotension.

Intramuscular Administration

If given intramuscularly, the recommended dose of Desferal is 500 mg to 1,000 mg per day. The maximum recommended daily dose is 1,000 mg per day.

2.3 Preparation

Reconstitute Desferal prior to administration. Desferal should be further diluted for intravenous infusion. Use appropriate aseptic technique.

Reconstitute each vial of Desferal with Sterile Water for Injection, USP per Table 1. Parenteral drug products should be inspected visually for particulate matter and discoloration prior to administration, whenever solution and container permit. Do not use if visibly opaque particles, discoloration or foreign particles are observed. The reconstituted Desferal solution is an isotonic, clear and colorless to slightly-yellowish solution. Discard unused portion.

Table 1. Preparation of Desferal Prior to Administration
Vial size | Route of administration | Amount of Sterile Water for Injection, USP for reconstitution | Concentration after reconstitution
500 mg | Intramuscular | 2 mL | 213 mg/mL
500 mg | Intravenous* | 5 mL | 95 mg/mL**
500 mg | Subcutaneous | 5 mL | 95 mg/mL
*Intravenous route of administration requires further dilution with 150 mL of 0.9% Sodium Chloride Injection, USP or 0.45% Sodium Chloride Injection, USP or 5% Dextrose Injection, USP or Lactated Ringers Injection, USP.
**Final concentration for intravenous administration is between 3 mg/mL to 3.5 mg/mL.

If not used immediately, store at room temperature between 20°C to 25°C (68°F to 77°F), excursions permitted between 15°C and 30°C (59°F and 86°F), for a maximum period of 24 hours. Do not refrigerate reconstituted solution.

2.4 Management of Vitamin C Deficiency

Patients with iron overload usually become vitamin C deficient, probably because iron oxidizes the vitamin. As an adjuvant to iron chelation therapy, vitamin C in doses up to 200 mg for adults may be given in divided doses, starting after an initial month of regular treatment with Desferal [see Warnings and Precautions (5.7)]. Vitamin C increases availability of iron for chelation. In general, 50 mg daily suffices for pediatric patients under 10 years old and 100 mg daily for older pediatric patients. Larger doses of vitamin C fail to produce any additional increase in excretion of iron complex.

3 DOSAGE FORMS AND STRENGTHS

For injection: 500 mg of deferoxamine mesylate (corresponding to 426.82 mg of deferoxamine as free base) as a white to almost white lyophilized powder in a single-dose vial for reconstitution.

4 CONTRAINDICATIONS

Desferal is contraindicated in patients with:

- A history of a hypersensitivity reaction to deferoxamine or any of its inactive ingredients [see Description (11)]. Reactions have included anaphylaxis [see Warnings and Precautions (5.1)].
- Severe renal disease or anuria since the drug and the iron chelate are excreted primarily by the kidney [see Warnings and Precautions (5.3)].

5 WARNINGS AND PRECAUTIONS

5.1 Hypersensitivity Reactions

Hypersensitivity reactions, including anaphylaxis, have occurred in Desferal-treated patients. Reactions have included flushing of the skin, urticaria, hypotension, and shock. These reactions typically occur when Desferal was administered by rapid intravenous injection. Therefore, administer Desferal intramuscularly or by slow subcutaneous or intravenous infusion.

5.2 Auditory and Ocular Toxicity

Ocular and auditory toxicities have been reported in Desferal-treated patients. The ocular toxicities observed have included blurring of vision; cataracts after prolonged administration in chronic iron overload; decreased visual acuity, including visual loss, visual defects, scotoma; impaired peripheral, color, and night vision; optic neuritis, cataracts, corneal opacities, and retinal pigmentary abnormalities. The auditory toxicities reported have been tinnitus and hearing loss, including high frequency sensorineural hearing loss. Risk factors for both ocular and auditory disturbances include prolonged treatment duration, higher doses, or low ferritin levels. In most cases, both ocular and auditory disturbances were reversible upon immediate cessation of treatment [see Adverse Reactions (6)].

Visual acuity tests, slit-lamp examinations, funduscopy, and audiometry are recommended periodically in patients treated for prolonged periods of time. Toxicity is more likely to be reversed if symptoms or test abnormalities are detected early.

5.3 Renal Toxicity

Renal toxicity, including increases in serum creatinine (possibly dose-related), acute renal failure and renal tubular disorders has occurred in Desferal-treated patients. Desferal is contraindicated in patients with severe renal disease [see Contraindications (4)]. Monitor serum creatinine to assess for changes in renal function.

5.4 Respiratory Toxicity

Acute respiratory distress syndrome has occurred in Desferal-treated patients following treatment with excessively high intravenous doses of Desferal in patients with acute iron intoxication or thalassemia. The recommended daily doses should therefore not be exceeded.

5.5 Growth Suppression

High doses of Desferal and concomitant low ferritin levels have also been associated with growth suppression in pediatric patients. After reduction of Desferal dose, growth velocity may partially resume to pre-treatment rates. Monitor growth (weight and height) in pediatric patients treated with Desferal every 3 months.

5.6 Serious Infections

Yersinia Infections

Desferal may increase the risk of Yersinia enterocolitica and Yersinia pseudotuberculosis infections. Avoid starting Desferal treatment in patients with active Yersinia infections. Should Yersinia infection develop, interrupt Desferal treatment until the infection is resolved.

Mucormycosis

Cases of mucormycosis, some with a fatal outcome, have occurred in Desferal-treated patients. Signs or symptoms are specific to the site of infection. If mucormycosis is suspected, discontinue Desferal, conduct mycological testing, and treat immediately.

5.7 Cardiac Dysfunction With Concomitant Use of Vitamin C

Cardiac dysfunction has occurred in Desferal-treated patients with severe chronic iron overload following concomitant treatment with high doses of vitamin C (more than 500 mg daily in adults). The cardiac dysfunction was reversible when vitamin C was discontinued. The following precautions should be taken when vitamin C and Desferal are to be used concomitantly:

- Vitamin C supplements should not be given to patients with cardiac failure.
- Start supplemental vitamin C only after an initial month of regular treatment with Desferal.
- Give vitamin C only if the patient is receiving Desferal regularly, ideally soon after setting up the infusion pump.
- Do not exceed a daily vitamin C dose of 200 mg in adults, given in divided doses. In general, 50 mg daily suffices for pediatric patients under 10 years old and 100 mg for older pediatric patients.
- Clinical monitoring of cardiac function is advisable during such combined therapy.

5.8 Risks of Desferal Treatment in Patients With Aluminum Overload

Desferal may cause neurological dysfunction (including seizures) in patients with aluminum-related encephalopathy and receiving dialysis, possibly due to an acute increase in circulating aluminum [see Adverse Reactions (6)].

Desferal may precipitate the onset of dialysis dementia.

Treatment with Desferal in the presence of aluminum overload may result in decreased serum calcium and aggravation of hyperparathyroidism.

5.9 Effects on Ability to Drive and Use Machines

Desferal may cause dizziness, which may impair the ability to drive a car or operate machinery. Patients should not drive or operate machinery until they know how Desferal will affect their ability to engage in these activities.

5.10 Embryo-Fetal Toxicity

Based on findings in animals, Desferal can cause fetal harm when administered to a pregnant woman. In animal reproduction studies, administration of deferoxamine to pregnant mice and rabbits during the period of organogenesis caused adverse developmental outcomes including decreased fetal body weights and malformations at maternal doses less than those in patients at maximum recommended human dose (MRHD). Advise pregnant women of the potential risk to a fetus. Advise females of reproductive potential and males with female partners of reproductive potential to use effective contraception during treatment with Desferal and for one month after the last dose [see Use in Specific Populations (8.1, 8.3), Nonclinical Toxicology (13.1)].

6 ADVERSE REACTIONS

The following clinically significant adverse reactions are described elsewhere in the labeling:

- Hypersensitivity Reactions [see Warnings and Precautions (5.1)]
- Auditory and Ocular Toxicity [see Warnings and Precautions (5.2)]
- Renal Toxicity [see Warnings and Precautions (5.3)]
- Respiratory Toxicity [see Warnings and Precautions (5.4)]
- Growth Suppression [see Warnings and Precautions (5.5)]
- Serious Infections [see Warnings and Precautions (5.6)]
- Cardiac Dysfunction with Concomitant Use of Vitamin C [see Warnings and Precautions (5.7)]
- Risks of Desferal Treatment in Patients with Aluminum Overload [see Warnings and Precautions (5.8)]
- Effects on Ability to Drive and Use Machines [see Warnings and Precautions (5.9)]

6.1 Clinical Trials Experience

The following adverse reactions associated with the use of Desferal were identified in clinical studies or postmarketing reports. Because some of these reactions were reported voluntarily from a population of uncertain size, it is not always possible to reliably estimate their frequency or establish a causal relationship to drug exposure.

At the Injection Site: Localized irritation, pain, burning, swelling, induration, infiltration, pruritus, erythema, wheal formation, eschar, crust, vesicles, local edema. Injection site reactions may be associated with systemic allergic reactions (see Body as a Whole, below).

Hypersensitivity Reactions and Systemic Allergic Reactions: Generalized rash, urticaria, anaphylactic reaction with or without shock, angioedema

Body as a Whole: Local injection site reactions may be accompanied by systemic reactions like arthralgia, fever, headache, myalgia, nausea, vomiting, abdominal pain, or asthma

Infections: Yersinia, mucormycosis

Cardiovascular: Tachycardia, hypotension, shock

Digestive: Abdominal discomfort, diarrhea, nausea, vomiting

Hematologic: Blood dyscrasia (thrombocytopenia, leucopenia)

Hepatic: Increased transaminases, hepatic dysfunction

Musculoskeletal: Muscle spasms. Growth retardation and bone changes (e.g., metaphyseal dysplasia)

Nervous System: Neurological disturbances, including dizziness, peripheral sensory, motor, or mixed neuropathy, paresthesias, seizures; exacerbation or precipitation of aluminum-related dialysis encephalopathy

Special Senses: High-frequency sensorineural hearing loss, tinnitus visual disturbances including acuity, blurred vision, loss of vision, dyschromatopsia, night blindness, visual field defects, scotoma, retinopathy (pigmentary degeneration), optic neuritis, and cataracts

Respiratory: Acute respiratory distress syndrome (with dyspnea, cyanosis, and/or interstitial infiltrates)

Skin: Generalized rash

Urogenital: Dysuria, acute renal failure, increased serum creatinine, and renal tubular disorders

7 DRUG INTERACTIONS

7.1 Prochlorperazine

Concurrent treatment with Desferal and prochlorperazine, a phenothiazine derivative, may lead to temporary impairment of consciousness.

7.2 Gallium-67

Imaging results may be distorted because of the rapid urinary excretion of Desferal-bound gallium-67. Discontinue Desferal 48 hours prior to scintigraphy.

8 USE IN SPECIFIC POPULATIONS

8.1 Pregnancy

Risk Summary

There are no available data on Desferal use in pregnant women to evaluate for a drug-associated risk of major birth defects, miscarriages or adverse maternal or fetal outcomes.

In animal reproduction studies subcutaneous administration of deferoxamine to pregnant animals (mice or rabbits) during organogenesis at doses approximately ≥ 0.2 (mice) and ≥ 0.7 (rabbits) times the maximum recommended human dose resulted in maternal toxicity and adverse developmental outcomes (see Data). Advise pregnant women of the potential risk to a fetus. Consider the benefits and risks of Desferal for the mother and possible risks to the fetus when prescribing Desferal to a pregnant woman.

The estimated background risk of major birth defects and miscarriage for the indicated population(s) is unknown. All pregnancies have a background risk of birth defect, loss, or other adverse outcomes. In the U.S. general population, the estimated background risk of major birth defects and miscarriage in clinically recognized pregnancies is 2% to 4% and 15% to 20%, respectively.

Data

Animal Data

In an embryo-fetal developmental study in mice, pregnant animals administered subcutaneous doses of deferoxamine at 180, and 540 mg/kg/day from gestation day 7 to gestation day 12 resulted in a dose dependent delay and irregularities of fetal skeletal maturation at doses ≥ 0.2 times the MRHD. At the highest dose of 540 mg/kg, in 1/23 fetuses had a unilateral lesion to the eye lens (approximately 0.5 times the MRHD).

In the embryo-fetal developmental studies in rabbits, pregnant animals administered subcutaneous doses of deferoxamine either 200 mg/kg or 200, 300, and 540 mg/kg from gestation day 6 to gestation day 14 resulted in maternal toxicity and embryo-fetal developmental effects at 0.7 times the MRHD). Maternal toxicity included reduced fetal body weights and embryo-fetal effects included malformations of spina bifida, and increased incidence of abnormally ossified ribs and vertebrae.

No maternal toxicity or embryo-fetal effects were observed in rats at deferoxamine doses tested (up to 0.9 times the MRHD).

8.2 Lactation

There are no data on the presence of deferoxamine or its metabolite in either human or animal milk, the effects on the breastfed child, or the effects on milk production. It is not known whether deferoxamine is excreted in human milk. Because of the potential for serious adverse reactions in the breastfed child, advise patients not to breastfeed during treatment with Desferal, and for one week after the last dose.

8.3 Females and Males of Reproductive Potential

Based on animal data, Desferal can cause malformations at doses less than the human dose [see Use in Specific Populations (8.1)].

Contraception

Females

Desferal can cause embryo-fetal harm when administered to pregnant women [see Use in Specific Populations (8.1)]. Advise female patients of reproductive potential to use effective contraception during treatment with Desferal and for one month after the last dose.

8.4 Pediatric Use

Safety and effectiveness in pediatric patients 3 years of age and older have been established for the treatment of acute iron intoxication and for the treatment of transfusional iron overload in patients with chronic anemia. Safety and effectiveness in pediatric patients under the age of 3 years have not been established.

Iron mobilization with Desferal is relatively poor in patients under the age of 3 years with relatively little iron overload. Desferal is not recommended for use. The drug should ordinarily not be given to these patients unless significant iron mobilization (e.g., 1 mg or more of iron per day) can be demonstrated.

High doses of Desferal and concomitant low ferritin levels have been associated with growth suppression in pediatric patients. Monitor weight and height in pediatric patients receiving Desferal every 3 months [see Warnings and Precautions (5.5), Adverse Reactions (6.1)].

8.5 Geriatric Use

Clinical Studies of Desferal did not include sufficient numbers of subjects aged 65 years and over to determine whether they respond differently from the younger subjects. Postmarketing reports suggest a possible trend for an increased risk of eye disorders in the geriatric population, specifically the occurrence of color blindness, maculopathy, and scotoma. However, it is unclear if these eye disorders were dose related. Although the number of reports was very small, certain elderly patients may be predisposed to eye disorders when taking Desferal. Postmarketing reports also suggest that there may be an increased risk of deafness and hearing loss in the geriatric population [see Adverse Reactions (6)]. In general, dose selection for an elderly patient should be cautious, usually starting at the low end of the dosing range, reflecting the greater frequency of decreased hepatic, renal, or cardiac function, and of concomitant disease or other drug therapy.

8.6 Renal Impairment

Desferal is contraindicated in patients with severe renal disease [see Contraindications (4)].

For patients with renal impairment, dose selection should usually start at the low end of the dosing range.

Deferoxamine can cause increases in serum creatinine (possibly dose-related), acute renal failure and renal tubular disorders [see Warnings and Precautions (5.3)]. Monitor patients for changes in renal function.

8.7 Hepatic Impairment

For patients with hepatic impairment, dose selection should usually start at the low end of the dosing range.

10 OVERDOSAGE

Acute Toxicity

Intravenous LD50s (mg/kg): mice, 287; rats, 329.

Inadvertent administration of an overdose or inadvertent intravenous bolus administration/rapid intravenous infusion may be associated with hypotension, tachycardia and gastrointestinal disturbances; acute but transient loss of vision, aphasia, agitation, headache, nausea, pallor, CNS depression, including coma, bradycardia, and acute renal failure have been reported.

Acute respiratory distress syndrome has been reported following treatment with excessively high intravenous doses of Desferal in patients with acute iron intoxication and in patients with thalassemia.

There is no specific antidote for Desferal overdose. In case of overdose, discontinue Desferal and provide symptomatic supportive care.

Desferal is readily dialyzable.

11 DESCRIPTION

Desferal, deferoxamine mesylate, is an iron-chelating agent, available in vials for injection via intramuscular, subcutaneous, and intravenous administration. Desferal is supplied as vials containing 500 mg of deferoxamine mesylate USP (corresponding to 426.82 mg of deferoxamine as free base) in sterile, lyophilized form. Deferoxamine mesylate is N-[5-[3-[(5-aminopentyl)hydroxycarbamoyl]propionamido]pentyl]-3-[[5-(N-hydroxyacetamido)pentyl]carbamoyl]propionohydroxamic acid monomethanesul-fonate (salt), and its structural formula is:

Deferoxamine mesylate USP is a white to almost white powder. It is freely soluble in water and slightly soluble in methanol. Its molecular weight is 656.79 g/mol.

12 CLINICAL PHARMACOLOGY

12.1 Mechanism of Action

Desferal chelates iron by forming a stable complex that prevents the iron from entering into further chemical reactions. It readily chelates iron from ferritin and hemosiderin but not readily from transferrin; it does not combine with the iron from cytochromes and hemoglobin.

Desferal does not cause any demonstrable increase in the excretion of electrolytes or trace metals. Theoretically, 100 parts by weight of Desferal is capable of binding approximately 8.5 parts by weight of ferric iron.

12.3 Pharmacokinetics

Desferal is metabolized principally by plasma enzymes, but the pathways have not yet been defined. The chelate is readily soluble in water and passes easily through the kidney, giving the urine a characteristic reddish color. Some is also excreted in the feces via the bile.

13 NONCLINICAL TOXICOLOGY

13.1 Carcinogenesis, Mutagenesis, Impairment of Fertility

Long-term carcinogenicity studies in animals have not been performed with Desferal. Cytotoxicity may occur, since Desferal has been shown to inhibit DNA synthesis in vitro.

Desferal was not mutagenic when tested in an in vitro bacterial reverse mutation (Ames) and was not genotoxic in an in vivo micronucleus assay in rats.

Animal studies to assess fertility effects have not been conducted.

16 HOW SUPPLIED/STORAGE AND HANDLING

How Supplied

Desferal is supplied in single-dose vials containing 500 mg of deferoxamine mesylate (corresponding to 426.82 mg of deferoxamine as free base) as a sterile, white to almost white lyophilized powder. Desferal is supplied in cartons of 4 vials (NDC 0078-0467-91).

Storage and Handling

Store at 20°C to 25°C (68°F to 77°F), excursions permitted between 15°C and 30°C (59°F and 86°F).

17 PATIENT COUNSELING INFORMATION

Caution patients about the potential allergic reactions associated with rapid intravenous administration of Desferal and the need for monitoring allergic reactions during treatment [see Warnings and Precautions (5.1)].

Caution patients about the potential auditory and ocular toxicities due to prolonged use of Desferal, conduct auditory testing and ophthalmic testing at regular intervals. Advise patients to contact their healthcare provider if they develop visual or auditory changes during treatment [see Warnings and Precautions (5.2)].

Caution patients about the potential for kidney toxicity when taking Desferal and the need for kidney function test to monitor for increase in serum creatinine [see Warnings and Precautions (5.3)].

Inform patients that if they have difficulty in breathing during treatment, they should inform the health care provider as this is a symptom of acute respiratory distress syndrome which can occur with excessively high intravenous doses of Desferal [see Warnings and Precautions (5.4)].

Caution pediatric patients and their caregivers that child treated with Desferal could have slower than normal growth and the need to monitor for body weight and height every 3 months [see Warnings and Precautions (5.5)].

Caution patients about the increased risk of bacterial infections (Yersinia enterocolitica and Yersinia pseudotuberculosis) with Desferal treatment and the need for treatment discontinuation until the infection is resolved [see Warnings and Precautions (5.6)].

Caution patients about the potential risk of fungal infections (Mucormycosis) when receiving Desferal treatment and the need for treatment discontinuation, mycological tests and required treatment for treating the infection [see Warnings and Precautions (5.6)].

Caution patients about the potential impairment of cardiac function when taking Desferal concomitantly with high doses of Vitamin C (more than 500 mg daily in adults). Inform adult patients not to exceed a daily Vitamin C dose of 200 mg given in divided doses. Inform pediatric patients under 10 years of age and older pediatric patients or their care takers not to exceed a daily Vitamin C of 50 mg and 100 mg, respectively. [see Dosage and Administration (2.4) and Warnings and Precautions (5.7)].

Inform patients with cardiac failure not to take Vitamin C supplements when on treatment with Desferal [see Dosage and Administration (2.4) and Warnings and Precautions (5.7)].

Caution patients with aluminum-related encephalopathy and receiving dialysis about potential neurological dysfunction [see Warnings and Precautions (5.8)].

Cautions patients that treatment with Desferal in the presence of aluminum overload may result in decreased serum calcium and aggravation of hyperparathyroidism [see Warnings and Precautions (5.8)].

Inform patients that they should refrain from driving or operating potentially hazardous machines if they experience dizziness or other nervous system disturbances, or impairment of vision or hearing [see Warnings and Precautions (5.9)].

Advise patients to inform the healthcare provider if they have received prochlorperazine prior to Desferal treatment as this may lead to temporary impairment of consciousness [see Drug Interactions (7.1)].

Inform patients that if they are going for any imaging tests while receiving Gallium-67 and Desferal concomitantly it can result in reports with distorted images [see Drug Interactions (7.2)].

Inform patients that their urine may occasionally show a reddish discoloration.

Embryo-fetal Toxicity:

Advise pregnant women and females of reproductive potential of the potential risk to a fetus. Advise females of reproductive potential to inform their healthcare provider of a known or suspected pregnancy [see Warnings and Precautions (5.10), Use in Specific Populations (8.1, 8.3)].

Advise females of reproductive potential to use effective contraceptive during treatment with Desferal and for one month after the last dose [see Use in Specific Populations (8.3)].

Lactation

Advise patients to avoid breastfeeding while taking Desferal and for one week after the final dose [see Use in Specific Populations (8.2)].

Distributed by:
Novartis Pharmaceuticals Corporation
East Hanover, New Jersey 07936

© Novartis

T2022-57

PRINCIPAL DISPLAY PANEL

NDC 0078-0467-91

NOVARTIS

Desferal®

deferoxamine mesylate for injection USP

500 mg per vial

Rx only

Each vial contains deferoxamine mesylate USP, 500 mg in lyophilized form.

For subcutaneous intramuscular or intravenous administration.

4 vials